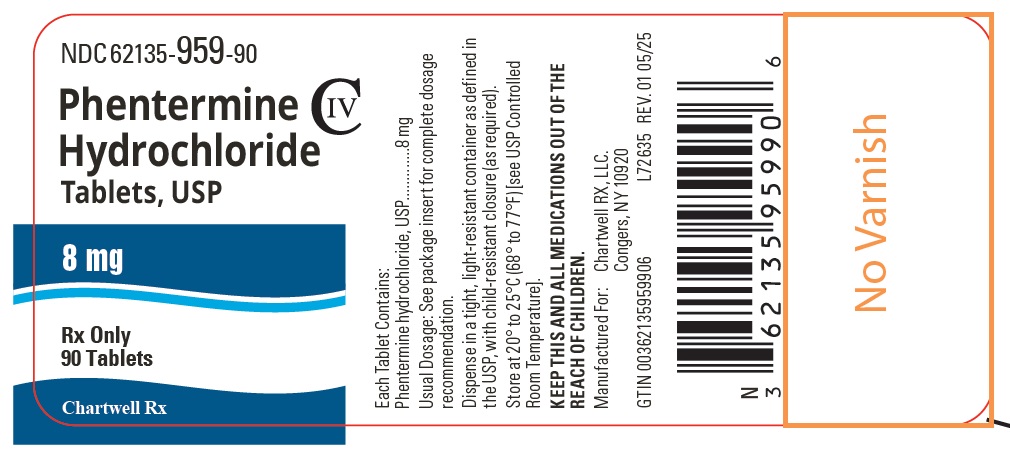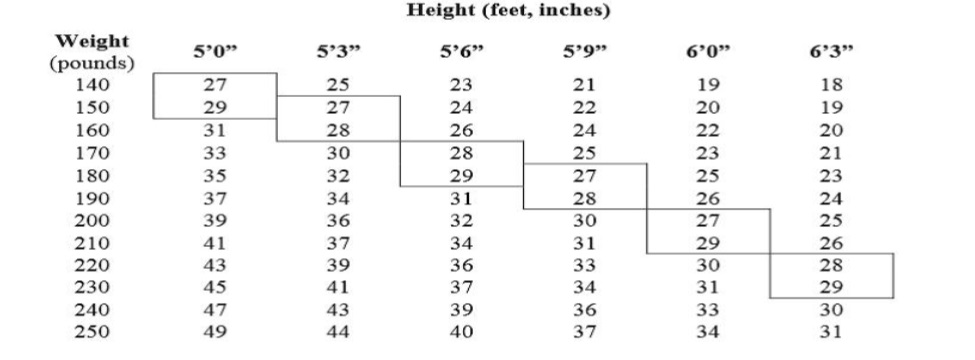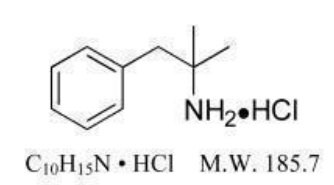 DRUG LABEL: Phentermine Hydrochloride
NDC: 62135-959 | Form: TABLET
Manufacturer: Chartwell RX, LLC
Category: prescription | Type: HUMAN PRESCRIPTION DRUG LABEL
Date: 20250819
DEA Schedule: CIV

ACTIVE INGREDIENTS: PHENTERMINE HYDROCHLORIDE 8 mg/1 1
INACTIVE INGREDIENTS: LACTOSE MONOHYDRATE; MICROCRYSTALLINE CELLULOSE; HYDROGENATED COTTONSEED OIL; MAGNESIUM STEARATE; SILICON DIOXIDE

Phentermine Hydrochloride Tablets, USP CIV

DESCRIPTION

Phentermine hydrochloride is a sympathomimetic amine anorectic. Its chemical name is α, α, -dimethylphenethylamine hydrochloride. The structural formula is as follows:

Phentermine hydrochloride is a white, odorless, hygroscopic, crystalline powder which is soluble in water and lower alcohols, slightly soluble in chloroform and insoluble in ether. Each 8 mg contains Phentermine Hydrochloride, USP, and inactive ingredients include hydrogenated vegetable oil, lactose monohydrate, microcrystalline cellulose, colloidal silicon dioxide and magnesium stearate.

CLINICAL PHARMACOLOGY

Mechanism of Action

Phentermine is a sympathomimetic amine with pharmacologic activity similar to the prototype drugs of this class used in obesity, amphetamine (d- and d/l-amphetamine). Drugs of this class used in obesity are commonly known as “anorectics” or “anorexigenics.” It has not been established that the primary action of such drugs in treating obesity is one of appetite suppression since other central nervous system actions, or metabolic effects, may also be involved.

Pharmacodynamics

Typical actions of amphetamines include central nervous system stimulation and elevation of blood pressure. Tachyphylaxis and tolerance have been demonstrated with all drugs of this class in which these phenomena have been looked for.

Pharmacokinetics

Specific Populations

Renal Impairment

Phentermine was not studied in patients with renal impairment. The literature reported cumulative urinary excretion of phentermine under uncontrolled urinary pH conditions is 62%-85%. Exposure increases can be expected in patients with renal impairment. Use 62%-85%. Exposure increases can be expected in patients with renal impairment. Use caution when administering phentermine to patients with renal impairment.

CLINICAL STUDIES

In relatively short-term clinical trials, adult obese subjects instructed in dietary management and treated with “anorectic” drugs lost more weight on the average than those treated with placebo and diet.

The magnitude of increased weight loss of drug-treated patients over placebo-treated patients is only a fraction of a pound a week. The rate of weight loss is greatest in the first weeks of therapy for both drug and placebo subjects and tends to decrease in succeeding weeks. The possible origins of the increased weight loss due to the various drug effects are not established. The amount of weight loss associated with the use of an “anorectic” drug varies from trial to trial, and the increased weight loss appears to be related in part to variables other than the drugs prescribed, such as the physician investigator, the population treated and the diet prescribed. Studies do not permit conclusions as to the relative importance of the drug and non-drug factors on weight loss.

The natural history of obesity is measured over several years, whereas the studies cited are restricted to a few weeks’ duration; thus, the total impact of drug-induced weight loss over that of diet alone must be considered clinically limited.

INDICATIONS AND USAGE

Phentermine hydrochloride tablets are indicated as a short-term (a few weeks) adjunct in a regimen of weight reduction based on exercise, behavioral modification and caloric restriction in the management of exogenous obesity in patients with an initial body mass index greater than or equal to 30 kg/m , or greater than or equal to 27 kg/m in the presence of other risk factors (e.g., controlled hypertension, diabetes, hyperlipidemia).

Below is a chart of body mass index (BMI) based on various heights and weights.

BMI is calculated by taking the patient’s weight, in kilograms (kg), divided by the patient’s height, in meters (m), squared. Metric conversions are as follows: pounds ÷ 2.2 = kg; inches x 0.0254 = meters.

BODY MASS INDEX (BMI), kg/m^2

The limited usefulness of agents of this class, including phentermine (see Clinical Pharmacology), should be measured against possible risk factors inherent in their use such as those described below.

CONTRAINDICATIONS

- History of cardiovascular disease (e.g., coronary artery disease, stroke, arrhythmias, congestive heart failure, uncontrolled hypertension)
- During or within 14 days following the administration of monoamine oxidase inhibitors
- Hyperthyroidism
- Glaucoma
- Agitated states
- History of drug abuse
- Pregnancy (see Precautions)
- Nursing (see Precautions)
- Known hypersensitivity, or idiosyncrasy to the sympathomimetic amines

WARNINGS

Coadministration with Other Drug Products for Weight Loss

Phentermine hydrochloride tablets are indicated only as short-term (a few weeks) monotherapy for the management of exogenous obesity. The safety and efficacy of combination therapy with phentermine and any other drug products for weight loss including prescribed drugs, over-the-counter preparations, and herbal products, or serotonergic agents such as selective serotonin reuptake inhibitors (e.g., fluoxetine, sertraline, fluvoxamine, paroxetine), have not been established. Therefore, coadministration of phentermine and these drug products is not recommended.

Primary Pulmonary Hypertension (PPH) – a rare, frequently fatal disease of the lungs – has been reported to occur in patients receiving a combination of phentermine with fenfluramine or dexfenfluramine. The possibility of an association between PPH and the use of phentermine alone cannot be ruled out; there have been rare cases of PPH in patients who reportedly have taken phentermine alone. The initial symptom of PPH is usually dyspnea. Other initial symptoms may include angina pectoris, syncope or lower extremity edema. Patients should be advised to report immediately any deterioration in exercise tolerance. Treatment should be discontinued in patients who develop new, unexplained symptoms of dyspnea, angina pectoris, syncope or lower extremity edema, and patients should be evaluated for the possible presence of pulmonary hypertension.

Valvular Heart Disease

Serious regurgitant cardiac valvular disease, primarily affecting the mitral, aortic and/or tricuspid valves, has been reported in otherwise healthy persons who had taken a combination of phentermine with fenfluramine or dexfenfluramine for weight loss. The possible role of phentermine in the etiology of these valvulopathies has not been established and their course in individuals after the drugs are stopped is not known. The possibility of an association between valvular heart disease and the use of phentermine alone cannot be ruled out; there have been rare cases of valvular heart disease in patients who reportedly have taken phentermine alone.

Development of Tolerance, Discontinuation in Case of Tolerance

When tolerance to the anorectant effect develops, the recommended dose should not be exceeded in an attempt to increase the effect; rather, the drug should be discontinued.

Effect on the Ability to Engage in Potentially Hazardous Tasks

Phentermine may impair the ability of the patient to engage in potentially hazardous activities such as operating machinery or driving a motor vehicle; the patient should therefore be cautioned accordingly.

Risk of Abuse and Dependence

Phentermine is related chemically and pharmacologically to amphetamine (d- and d/l-amphetamine) and other related stimulant drugs have been extensively abused. The possibility of abuse of phentermine should be kept in mind when evaluating the desirability of including a drug as part of a weight reduction program. See Adverse Reactions/ Drug Abuse and Dependenceand Overdosage.

The least amount feasible should be prescribed or dispensed at one time in order to minimize the possibility of overdosage.

Usage with Alcohol

Concomitant use of alcohol with phentermine may result in an adverse drug reaction.

Use in Patients with Hypertension

Use caution in prescribing phentermine for patients with even mild hypertension (risk of increase in blood pressure).

Use in Patients on Insulin or Oral Hypoglycemic Medications for Diabetes Mellitus

A reduction in insulin or oral hypoglycemic medications in patients with diabetes mellitus may be required.

PRECAUTIONS

Information for Patients

Patients must be informed that phentermine hydrochloride is a short-term (a few weeks) adjunct in a regimen of weight reduction based on exercise, behavioral modification and caloric restriction in the management of exogenous obesity, and that coadministration of phentermine with other drugs for weight loss is not recommended (see Indications and Usageand Warnings).

Patients must be instructed on how much phentermine to take, and when and how to take it (see Dosage and Administration).

Advise pregnant women and nursing mothers not to use phentermine (see Precautions).

Patients must be informed about the risks of use of phentermine (including the risks discussed in Warningsand Precautions), about the symptoms of potential adverse reactions and when to contact a physician and/or take other action. The risks include, but are not limited to:

- Development of primary pulmonary hypertension (see Warnings)
- Development of serious valvular heart disease (see Warnings)
- Effects on the ability to engage in potentially hazardous tasks (see Warnings)
- The risk of an increase in blood pressure (see Warningsand Adverse Reactions)
- The risk of interactions (see Contraindications, Warnings, and Precautions/ Drug Interactions)

The patients must also be informed about

- the potential for developing tolerance and actions if they suspect development of tolerance (see Warnings) and
- the risk of dependence and the potential consequences of abuse (see Warnings, Drug Abuse and Dependence, and Overdosage).

Tell patients to keep phentermine in a safe place to prevent theft, accidental overdose, misuse or abuse. Selling or giving away phentermine may harm others and is against the law.

Drug Interactions

Monoamine Oxidase Inhibitors

Use of phentermine is contraindicated during or within 14 days following the administration of monoamine oxidase inhibitors because of the risk of hypertensive crisis.

Alcohol

Concomitant use of alcohol with phentermine may result in an adverse drug reaction.

Insulin and Oral Hypoglycemic Medications

Requirements may be altered (see Warnings)

Adrenergic Neuron Blocking Drugs

Phentermine may decrease the hypotensive effect of adrenergic neuron blocking drugs.

Carcinogenesis, Mutagenesis, Impairment of Fertility

Studies have not been performed with phentermine to determine the potential for carcinogenesis, mutagenesis or impairment of fertility.

Pregnancy

Phentermine is contraindicated during pregnancy because weight loss offers no potential benefit to a pregnant woman and may result in fetal harm. A minimum weight gain, and no weight loss, is currently recommended for all pregnant women, including those who are already overweight or obese, due to obligatory weight gain that occurs in maternal tissues during pregnancy. Phentermine has pharmacologic activity similar to amphetamine (d- and d/l-amphetamine) (see Clinical Pharmacology). Animal reproduction studies have not been conducted with phentermine. If this drug is used during pregnancy, or if the patient becomes pregnant while taking this drug, the patient should be apprised of the potential hazard to a fetus.

Nursing Mothers

It is not known if phentermine is excreted in human milk; however, other amphetamines are present in human milk. Because of the potential for serious adverse reactions in nursing infants, a decision should be made whether to discontinue nursing or to discontinue the drug, taking into account the importance of the drug to the mother.

Pediatric Use

Safety and effectiveness in pediatric patients have not been established. Because pediatric obesity is a chronic condition requiring long-term treatment, the use of this product, approved for short-term therapy, is not recommended.

Geriatric Use

In general, dose selection for an elderly patient should be cautious, usually starting at the low end of the dosing range, reflecting the greater frequency of decreased hepatic, renal, or cardiac function, and of concomitant disease or other drug therapy.

This drug is known to be substantially excreted by the kidney, and the risk of toxic reactions to this drug may be greater in patients with impaired renal function. Because elderly patients are more likely to have decreased renal function, care should be taken in dose selection, and it may be useful to monitor renal function.

Renal Impairment

Phentermine was not studied in patients with renal impairment. Based on the reported excretion of phentermine in urine, exposure increases can be expected in patients with renal impairment. Use caution when administering phentermine to patients with renal impairment (see Clinical Pharmacology).

ADVERSE REACTIONS

The following adverse reactions are described, or described in greater detail, in other sections:

- Primary pulmonary hypertension (see Warnings)
- Valvular heart disease (see Warnings)
- Effect on the ability to engage in potentially hazardous tasks (see Warnings)
- Withdrawal effects following prolonged high dosage administration (see Drug Abuse and Dependence)

The following adverse reactions to phentermine have been identified:

Cardiovascular

Primary pulmonary hypertension and/or regurgitant cardiac valvular disease, palpitation, tachycardia, elevation of blood pressure, ischemic events.

Central Nervous System

Overstimulation, restlessness, dizziness, insomnia, euphoria, dysphoria, tremor, headache, psychosis.

Gastrointestinal

Dryness of the mouth, unpleasant taste, diarrhea, constipation, other gastrointestinal disturbances.

Allergic

Urticaria.

Endocrine

Impotence, changes in libido.

DRUG ABUSE AND DEPENDENCE

Controlled Substance

Phentermine is a Schedule IV controlled substance.

Abuse

Phentermine is related chemically and pharmacologically to the amphetamines. Amphetamines and other stimulant drugs have been extensively abused and the possibility of abuse of phentermine should be kept in mind when evaluating the desirability of including a drug as part of a weight reduction program.

Dependence

Abuse of amphetamines and related drugs may be associated with intense psychological dependence and severe social dysfunction. There are reports of patients who have increased the dosage of these drugs to many times than recommended. Abrupt cessation following prolonged high dosage administration results in extreme fatigue and mental depression; changes are also noted on the sleep EEG. Manifestations of chronic intoxication with anorectic drugs include severe dermatoses, marked insomnia, irritability, hyperactivity and personality changes. A severe manifestation of chronic intoxication is psychosis, often clinically indistinguishable from schizophrenia.

OVERDOSAGE

The least amount feasible should be prescribed or dispensed at one time in order to minimize the possibility of overdosage.

Acute Overdosage

Manifestations of acute overdosage include restlessness, tremor, hyperreflexia, rapid respiration, confusion, assaultiveness, hallucinations, and panic states. Fatigue and depression usually follow the central stimulation. Cardiovascular effects include arrhythmia, hypertension or hypotension, and circulatory collapse. Gastrointestinal symptoms include nausea, vomiting, diarrhea and abdominal cramps. Overdosage of pharmacologically similar compounds has resulted in fatal poisoning usually terminates in convulsions and coma.

Management of acute phentermine hydrochloride intoxication is largely symptomatic and includes lavage and sedation with a barbiturate. Experience with hemodialysis or peritoneal dialysis is inadequate to permit recommendations in this regard. Acidification of the urine increases phentermine excretion. Intravenous phentolamine (Regitine®, CIBA) has been suggested on pharmacologic grounds for possible acute, severe hypertension, if this complicates overdosage.

Chronic Intoxication

Manifestations of chronic intoxication with anorectic drugs include severe dermatoses, marked insomnia, irritability, hyperactivity and personality changes. The most severe manifestation of chronic intoxications is psychosis, often clinically indistinguishable from schizophrenia. See Drug Abuse and Dependence.

DOSAGE AND ADMINISTRATION

Dosage should be individualized to obtain an adequate response with the lowest effective dose.

The usual adult dose is one tablet three times a day ½ hour before meals. This tablet is scored to facilitate administering one half of the usual dosage for patients not requiring the full dose. Phentermine hydrochloride is not recommended for use in pediatric patients less than or equal to 16 years of age.

Late evening medication should be avoided because of the possibility of resulting insomnia.

HOW SUPPLIED/STORAGE AND HANDLING

Phentermine Hydrochloride Tablets, USP is supplied as white round scored tablets, debossed with " C" above the score line and " E" below on one side and " 263" on the other side.

Bottle of 90 tablets NDC 62135-959-90

Store at 20° to 25°C (68° to 77°F) [See USP Controlled Room Temperature].

Dispense in a tight container as defined in the USP, with a child-resistant closure (as required).

Keep out of the reach of children.

Manufactured for:
Chartwell RX, LLC.
Congers, NY 10920
L72636
Rev. 08/2025

PRINCIPAL DISPLAY PANEL

Phentermine Hydrochloride Tablets, USP CIV 8 mg - NDC 62135-959-90 - 90 Tabs Bottle Label